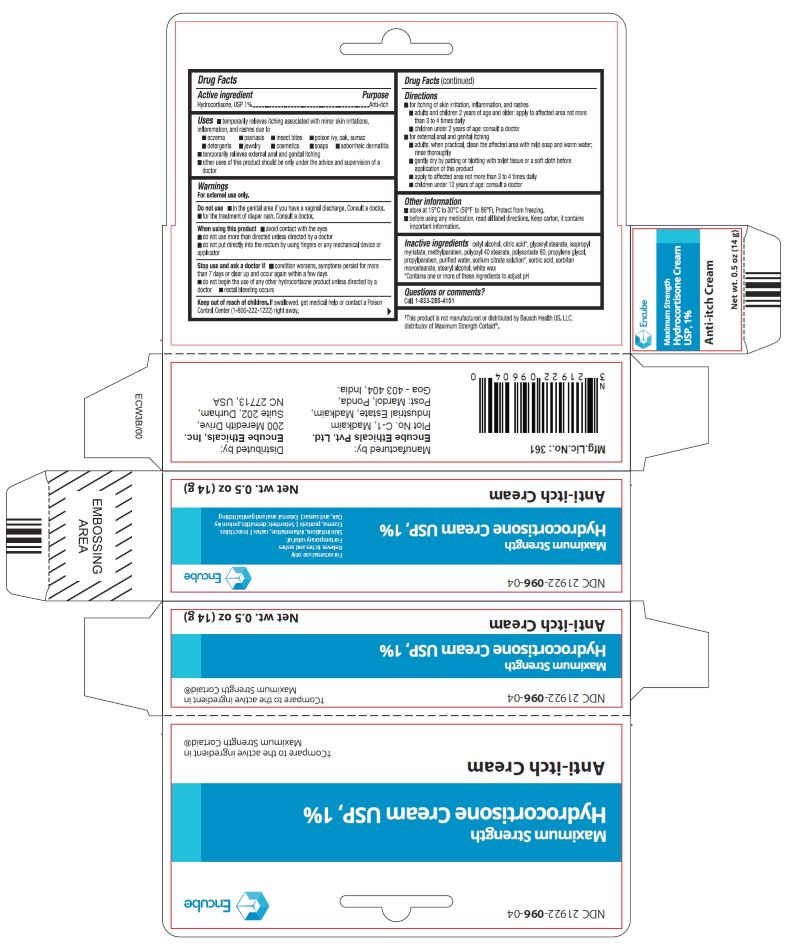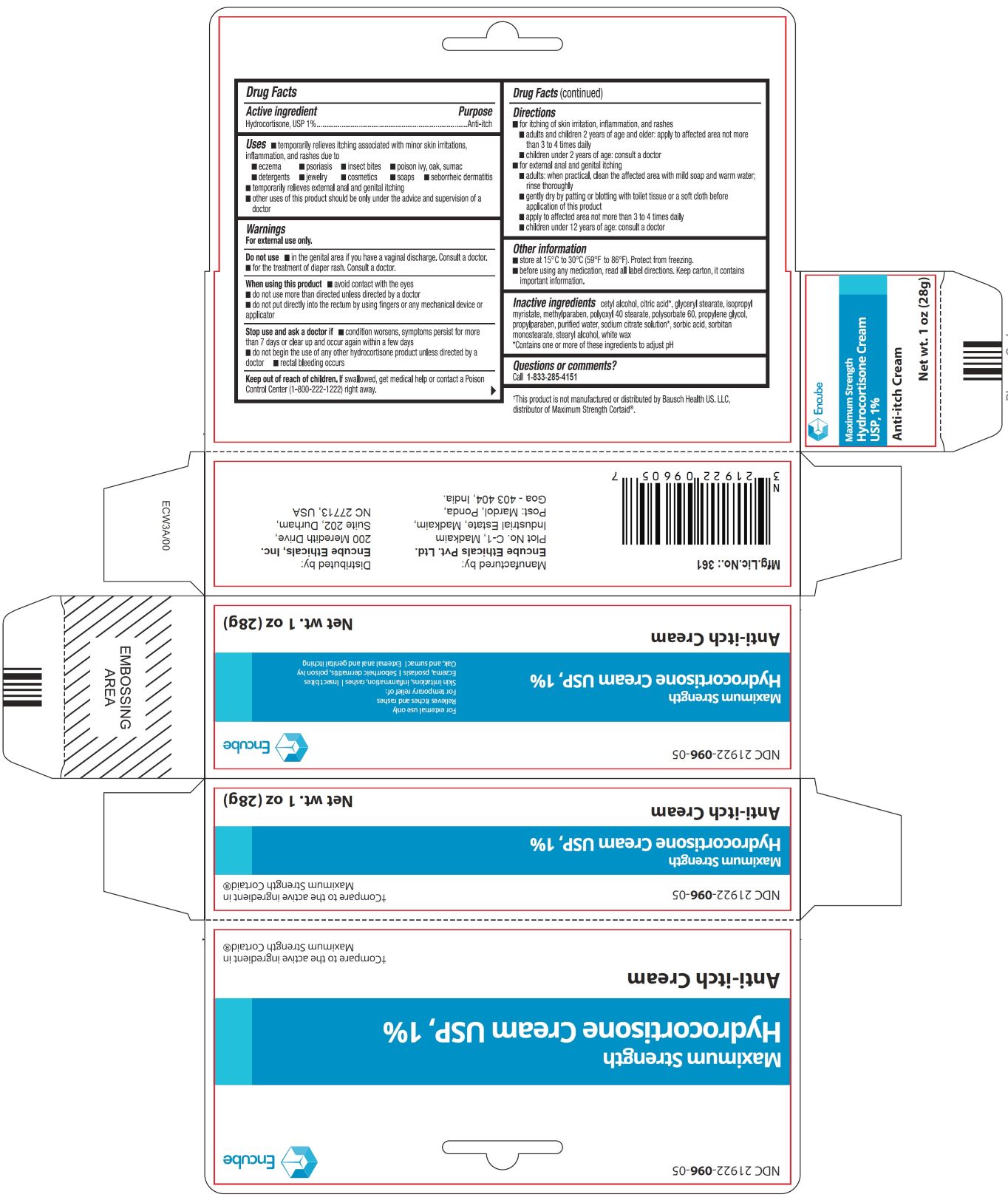 DRUG LABEL: HYDROCORTISONE
NDC: 21922-096 | Form: CREAM
Manufacturer: Encube Ethicals, Inc.
Category: otc | Type: Human OTC Drug Label
Date: 20251110

ACTIVE INGREDIENTS: HYDROCORTISONE 1 g/100 g
INACTIVE INGREDIENTS: CETYL ALCOHOL; CITRIC ACID MONOHYDRATE; GLYCERYL MONOSTEARATE; ISOPROPYL MYRISTATE; METHYLPARABEN; POLYOXYL 40 STEARATE; POLYSORBATE 60; PROPYLENE GLYCOL; PROPYLPARABEN; WATER; SODIUM CITRATE; SORBIC ACID; SORBITAN MONOSTEARATE; STEARYL ALCOHOL; WHITE WAX

HYDROCORTISONE CREAM USP, 1%

ACTIVE INGREDIENT(S)

Hydrocortisone, USP 1%

PURPOSE

Anti-itch

USE(S)

■temporarily relieves itching associated with minor skin irritations, inflammation, and rashes due to

■eczema ■ psoriasis ■ insect bites ■ poison ivy, oak, sumac

■detergents ■ jewelry ■ cosmetics ■ soaps ■ seborrheic dermatitis

■temporarily relieves external anal and genital itching

■other uses of this product should be only under the advice and supervision of a doctor

WARNINGS

For external use only.

DO NOT USE

■ in the genital area if you have a vaginal discharge. Consult a doctor.
■ for the treatment o1 diaper rash. Consult a doctor.

WHEN USING THIS PRODUCT

■ avoid contact with the eyes

■ do not use more than directed unless directed by a doctor

■ do not put directly into the rectum by using fingers or any mechanical device or isopropyl applicator

STOP USE AND ASK DOCTOR IF

■ condition worsens, symptoms persist for more than 7 days or clear up and occur again within a few days

■ do not begin the use of any other hydrocortisone product unless directed by a doctor

■ rectal bleeding occurs

KEEP OUT OF REACH OF CHILDREN

If swallowed, get medical help or contact a Poison Control Center (1-800-222-1222) right away.

DIRECTIONS

■ for itching of skin irritation, inflammation, and rashes

■ adults and children 2 years of age and older: apply to affected area not more than 3 to 4 times daily

■ children under 2 years of age: consult a doctor

■ for external anal and genital itching

■ adults: when practical, clean the affected area with mild soap and warm water; rinse thoroughly

■ gently dry by paling or blotting with toilet Issue or a soft cloth before application of this product

■ apply to affected area not more than 3 to 4 times daily

■ children under 12 years of age: consult a doctor

OTHER INFORMATION

■ store at 15°C to 30°C (59°F to 86°F). Protect from freezing.

■ before using any medication, read all label directions. Keep carton, it contains important information.

INACTIVE INGREDIENTS

cetyl alcohol, citric acid*, glyceryl stearate, isopropyl myristate, methylparaben, polyoxyl 40 stearate, polysorbate 60, propylene glycol, propylparaben, purified water, sodium citrate solution* sorbic acid, sorbitan monostearate, stearyl alcohol, white wax

*Contains one or more of these ingredients to adjust pH

QUESTIONS OR COMMENTS?

Call 1-833-285-4151

PRINCIPAL DISPLAY PANEL

Hydrocortisone Cream USP, 1%

Anti-itch Cream

Net wt. 1 oz (28g)

Hydrocortisone Cream USP, 1%

Anti-itch Cream

Net wt. 0.5 oz (14g)